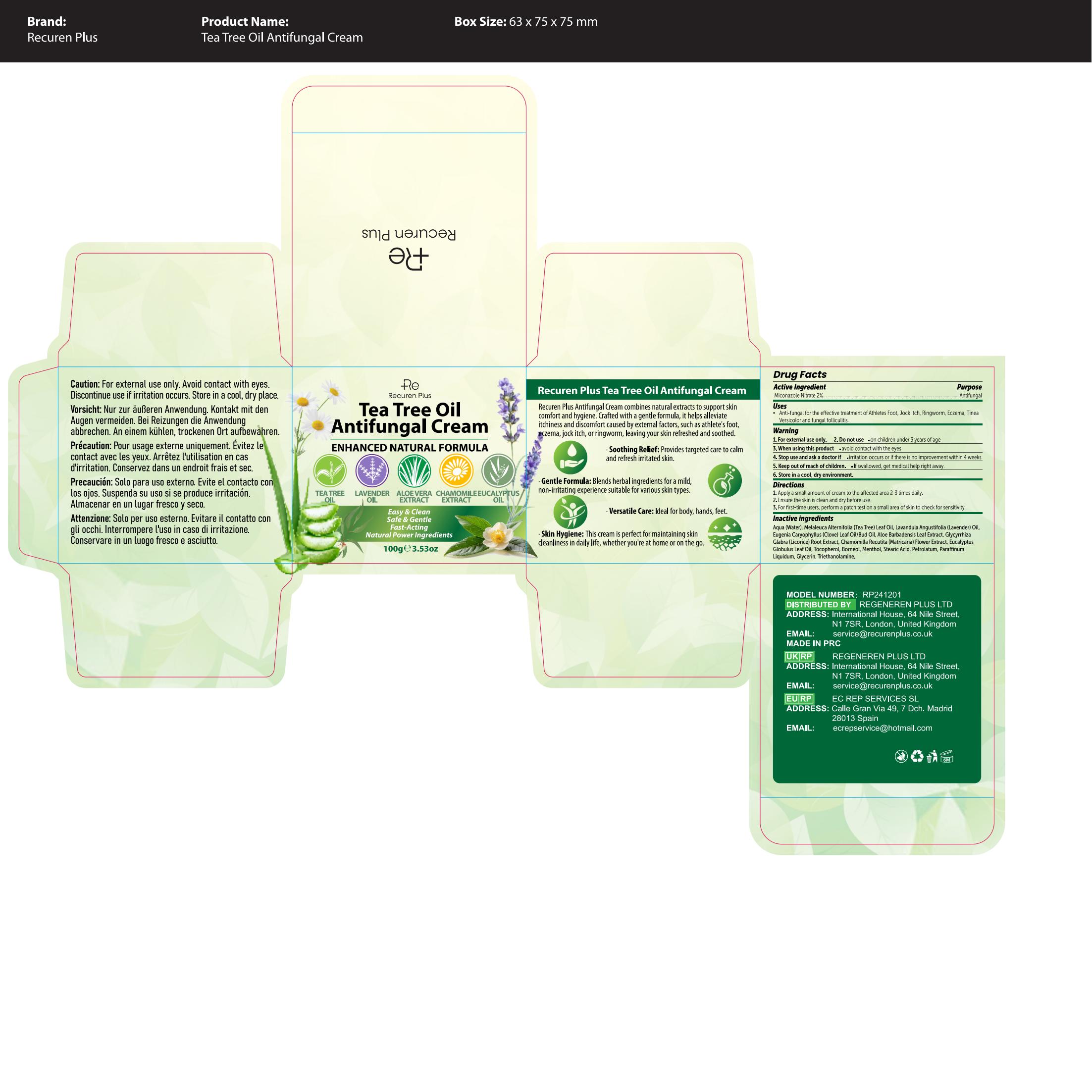 DRUG LABEL: Recuren Plus Antifungal Cream
NDC: 87014-001 | Form: CREAM
Manufacturer: REGENEREN PLUS LTD
Category: otc | Type: HUMAN OTC DRUG LABEL
Date: 20260212

ACTIVE INGREDIENTS: MICONAZOLE NITRATE 20 mg/1 g
INACTIVE INGREDIENTS: CLOVE OIL; TOCOPHEROL; AQUA; ALOE VERA LEAF OIL; STEARIC ACID; MENTHOL; BORNEOL; TEA TREE OIL; MATRICARIA RECUTITA FLOWERING TOP; PETROLATUM; PARAFFINUM LIQUIDUM; GLYCERIN; EUCALYPTUS GLOBULUS LEAF OIL; TRIETHANOLAMINE; LICORICE; LAVENDER OIL

ACTIVE INGREDIENT

Miconazole Nitrate 2%

PURPOSE

Antifungal

INSTRUCTIONS FOR USE

Anti-fungal for the effective treatment of Athlete's Foot, Jock Itch, Ringworm, Eczema, Tinea Versicolor, and fungal folliculitis.

WARNINGS

For external use only

INDICATIONS AND USAGE

1 Apply a small amount of cream to the affected area 2-3 times daily; 2 Ensure the skin in clean and dry before use; 3 For first-time users, perform a patch test on a small area of skin to check for sensitivity.

INACTIVE INGREDIENT

Aqua (Water), Melaleuca Alternifolia (Tea Tree) Leaf Oil, Lavandula Angustifolia (Lavender) Oil, Eugenia Caryophyllus (Clove) Leaf Oil/Bud Oil,
Aloe Barbadensis Leaf Extract, Glycyrrhiza Glabra (Licorice) Root Extract,
Chamomilla Recutita (Matricaria) Flower Extract, Eucalyptus Globulus Leaf Oil, Tocopherol, Borneol, Menthol,
Stearic Acid, Petrolatum, Paraffinum Liquidum, Glycerin, Triethanolamine.

QUESTIONS

Please contact the email: service@recurenplus.co.uk

DOSAGE AND ADMINISTRATION

1 Apply a small amount of cream to the affected area 2-3 times daily; 2 Ensure the skin in clean and dry before use; 3 For first-time users, perform a patch test on a small area of skin to check for sensitivity.

Keep Out of Reach of Children